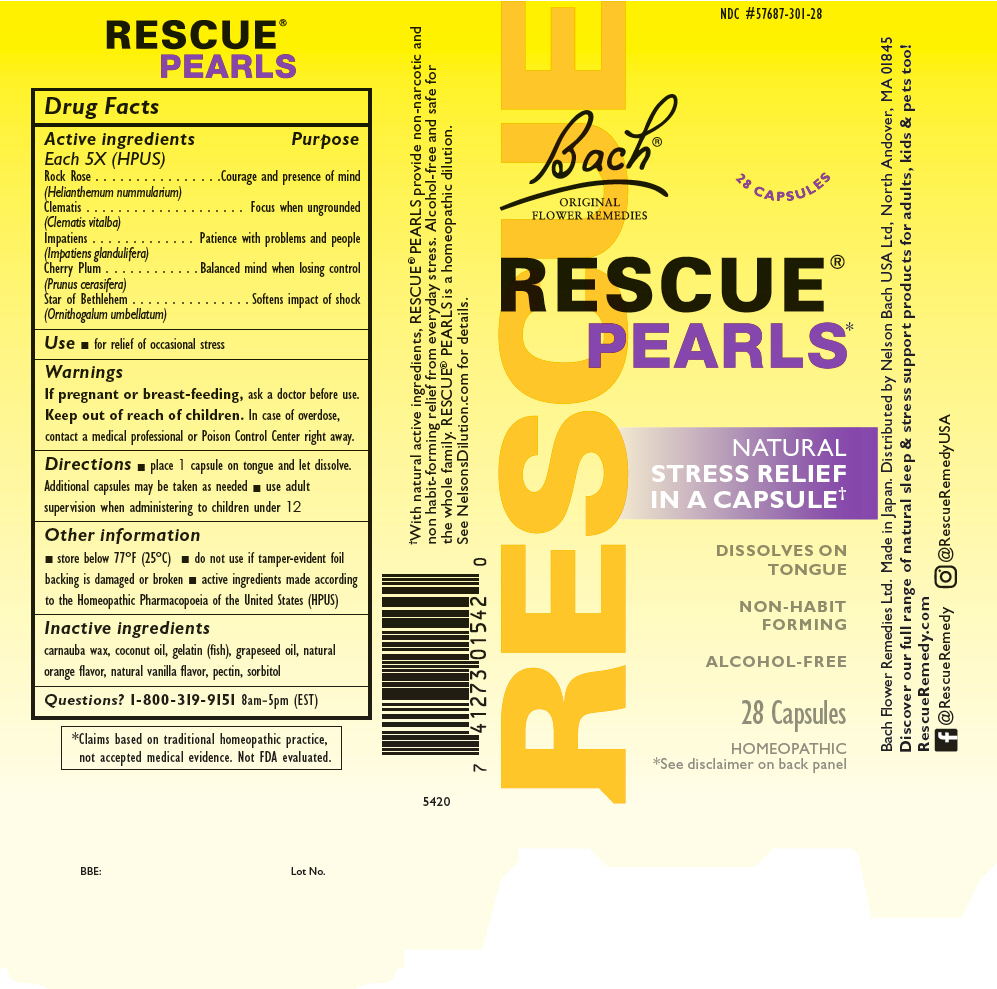 DRUG LABEL: Rescue Pearls
NDC: 57687-301 | Form: CAPSULE, LIQUID FILLED
Manufacturer: Nelson Bach USA, Ltd.
Category: homeopathic | Type: HUMAN OTC DRUG LABEL
Date: 20221006

ACTIVE INGREDIENTS: HELIANTHEMUM NUMMULARIUM FLOWER 5 [hp_X]/1 1; CLEMATIS VITALBA FLOWER 5 [hp_X]/1 1; IMPATIENS GLANDULIFERA FLOWER 5 [hp_X]/1 1; PRUNUS CERASIFERA FLOWER 5 [hp_X]/1 1; ORNITHOGALUM UMBELLATUM WHOLE 5 [hp_X]/1 1
INACTIVE INGREDIENTS: GRAPE SEED OIL; SORBITOL; CARNAUBA WAX; COCONUT OIL; PECTIN; MARINE NON-GELLING GELATIN, HIGH MW

Rescue® Pearls

Drug Facts

ACTIVE INGREDIENT

Active ingredients Each 5X (HPUS) | Purpose
Rock Rose (Helianthemum nummularium) | Courage and presence of mind
Clematis (Clematis vitalba) | Focus when ungrounded
Impatiens (Impatiens glandulifera) | Patience with problems and people
Cherry Plum (Prunus cerasifera) | Balanced mind when losing control
Star of Bethlehem (Ornithogalum umbellatum) | Softens impact of shock

Use

- for relief of occasional stress

Warnings

PREGNANCY OR BREAST FEEDING

If pregnant or breast-feeding, ask a doctor before use.

Keep out of reach of children. In case of overdose, contact a medical professional or Poison Control Center right away.

Directions

- place 1 capsule on tongue and let dissolve. Additional capsules may be taken as needed
- use adult supervision when administering to children under 12

Other information

- store below 77°F (25°C)
- do not use if tamper-evident foil backing is damaged or broken
- active ingredients made according to the Homeopathic Pharmacopoeia of the United States (HPUS)

Inactive ingredients

carnauba wax, coconut oil, gelatin (fish), grapeseed oil, natural orange flavor, natural vanilla flavor, pectin, sorbitol

Questions?

1-800-319-9151 8am-5pm (EST)

Distributed by Nelson Bach USA Ltd, North Andover, MA 01845

PRINCIPAL DISPLAY PANEL - 28 Capsule Blister Pack Carton

RESCUE

NDC #57687-301-28

Bach®
ORIGINAL
FLOWER REMEDIES

28 CAPSULES

RESCUE®
PEARLS*

NATURAL
STRESS RELIEF
IN A CAPSULE†

DISSOLVES ON
TONGUE

NON-HABIT
FORMING

ALCOHOL-FREE

28 Capsules

HOMEOPATHIC
*See disclaimer on back panel